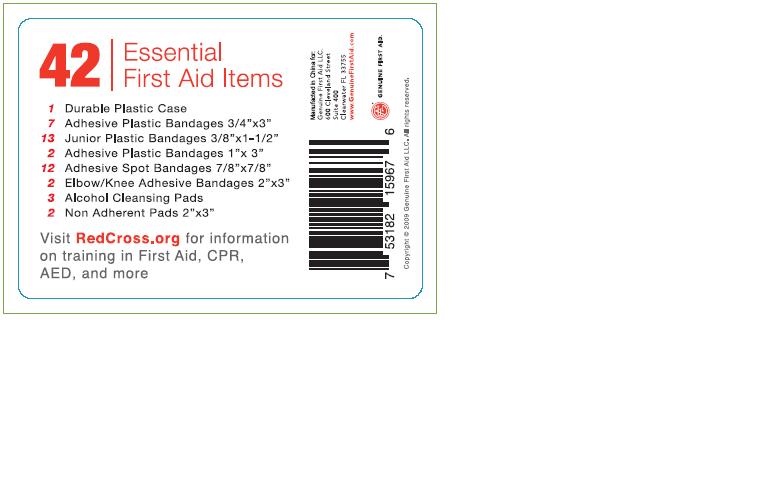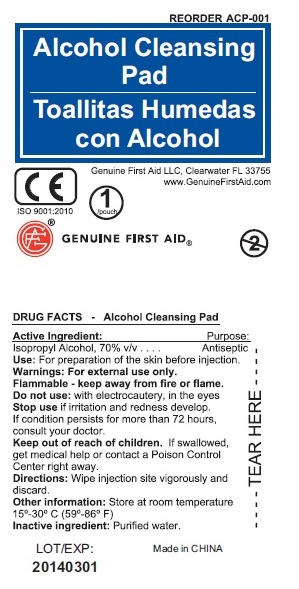 DRUG LABEL: ARC 42 Essential First Aid Items
NDC: 52164-1101 | Form: KIT | Route: TOPICAL
Manufacturer: American Red Cross
Category: otc | Type: HUMAN OTC DRUG LABEL
Date: 20100607

ACTIVE INGREDIENTS: ISOPROPYL ALCOHOL 70 mL/100 mL
INACTIVE INGREDIENTS: WATER

ARC 42 Essential First Aid Items

Active Ingredient: Purpose
Isopropyl Alcohol, 70% v/v............... Antiseptic

ACTIVE INGREDIENT

Use: For preparation of skin before injection.

Warnings: For external use only.

Do not use: with electrocautery, in the eyes.

WHEN USING

Wipe Injection site vigorously and discard.

Inactive Ingredient: Purified water.

DESCRIPTION

LOT/EXP: Made in CHINA
20140301

PACKAGE LABEL

Alcohol Cleansing Pad
Genuine First Aid LLC, Clearwater FL 33755
www.GenuineFirstAid.com
1/pouch
GENUINE FIRST AID

PACKAGE LABEL

42 Essential First Aid Items

1 Durable Plastic Case
7 Adhesive Plastic Bandages 3/4"x3"
13 Junior Plastic Bandages 3/8"x1-1/2"
2 Adhesive Plastic Bandages 1"x3"
12 Adhesive Spot Bandages 7/8"x7/8"
2 Elbow/Knee Adhesive Bandages 2"x3"
3 Alcohol Cleansing Pads
2 Non Adherent Pads 2"x3"

Visit RedCross.org for information on training in First Aid, CPR, AED, and more

Manufactured in China for:

Genuine First Aid LLC
600 Cleveland Street
Suite 400
Clearwater FL 34755

www.GenuineFirstAid.com

GENUINE FIRST AID

Copyright c 2009 Genuine First Aid LLC, All rights reserved.